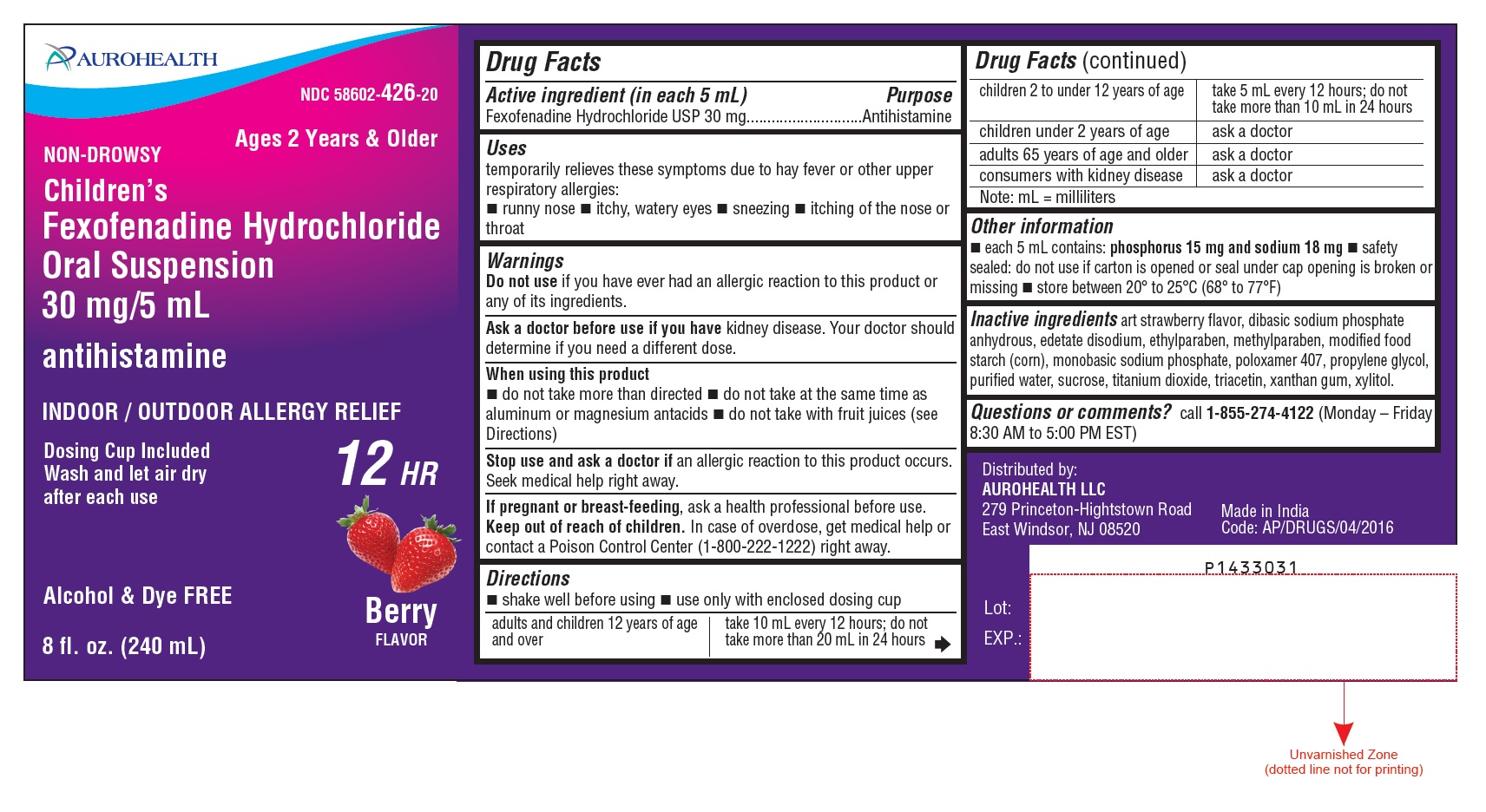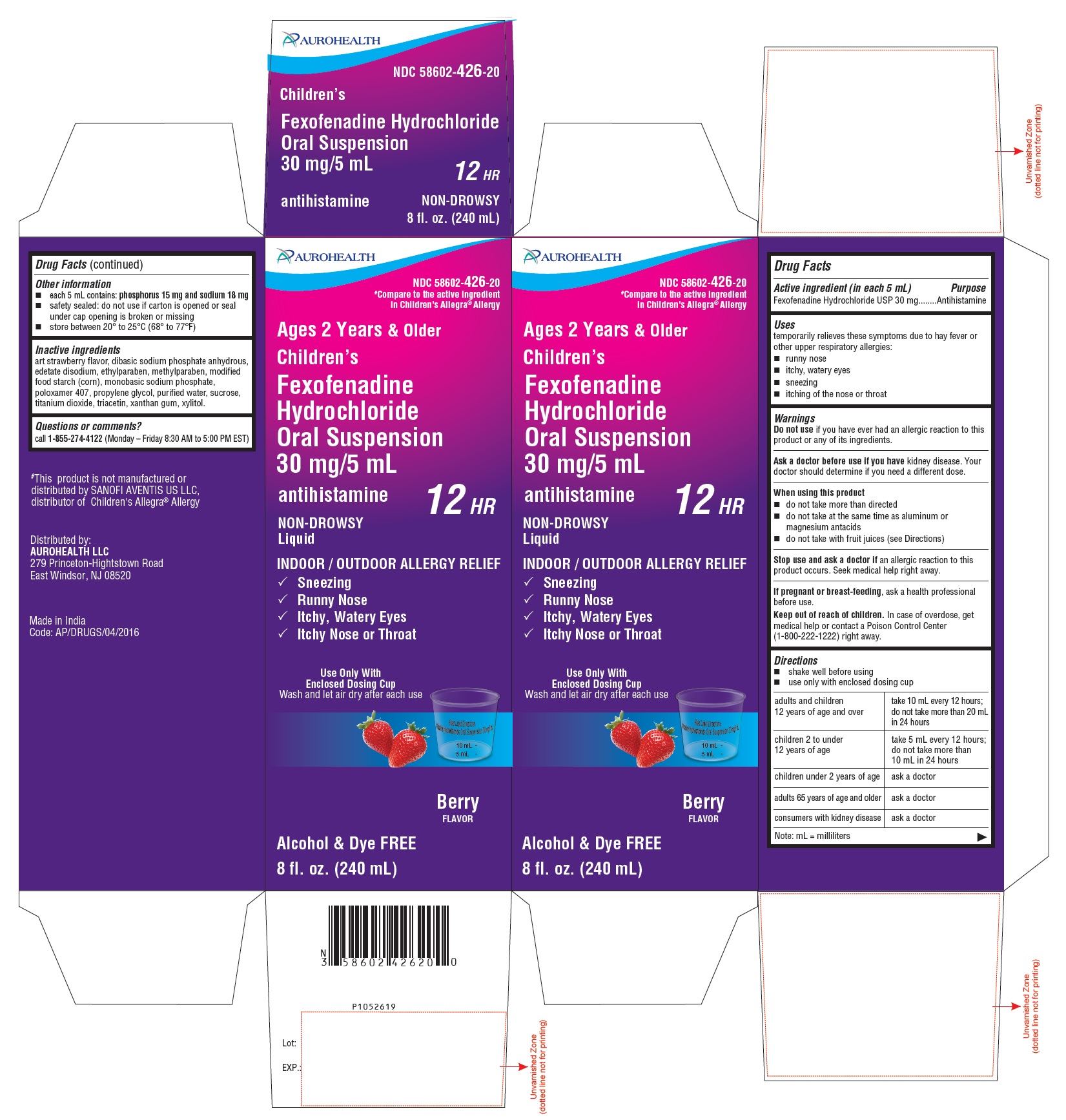 DRUG LABEL: Fexofenadine Hydrochloride
NDC: 58602-426 | Form: SUSPENSION
Manufacturer: Aurohealth LLC
Category: otc | Type: Human OTC Drug Label
Date: 20230606

ACTIVE INGREDIENTS: Fexofenadine Hydrochloride 30 mg/5 mL
INACTIVE INGREDIENTS: STRAWBERRY; SODIUM PHOSPHATE, DIBASIC, ANHYDROUS; EDETATE DISODIUM; ETHYLPARABEN; METHYLPARABEN; MODIFIED CORN STARCH (1-OCTENYL SUCCINIC ANHYDRIDE); SODIUM PHOSPHATE, MONOBASIC, MONOHYDRATE; POLOXAMER 407; PROPYLENE GLYCOL; WATER; SUCROSE; TITANIUM DIOXIDE; TRIACETIN; XANTHAN GUM; XYLITOL

Fexofenadine Hydrochloride Oral Suspension 30 mg/5 mL

Drug Facts

Active ingredient (in each 5 mL)

Fexofenadine Hydrochloride USP 30 mg

Purpose

Antihistamine

Uses

temporarily relieves these symptoms due to hay fever or other upper respiratory allergies:

- runny nose
- itchy, watery eyes
- sneezing
- itching of the nose or throat

Warnings

Do not use if you have ever had an allergic reaction to this product or any of its ingredients.

Ask a doctor before use if you have

kidney disease. Your doctor should determine if you need a different dose.

When using this product

- do not take more than directed
- do not take at the same time as aluminum or magnesium antacids
- do not take with fruit juices (see Directions)

Stop use and ask a doctor if

an allergic reaction to this product occurs. Seek medical help right away.

PREGNANCY OR BREAST FEEDING

If pregnant or breast-feeding, ask a health professional before use.

Keep out of reach of children.

In case of overdose, get medical help or contact a Poison Control Center (1-800-222-1222) right away.

Directions

- shake well before using
- use only with enclosed dosing cup

adults and children 12 years of age and over | take 10 mL every 12 hours; do not take more than 20 mL in 24 hours
children 2 to under 12 years of age | take 5 mL every 12 hours; do not take more than 10 mL in 24 hours
children under 2 years of age | ask a doctor
adults 65 years of age and older | ask a doctor
consumers with kidney disease | ask a doctor
Note: mL = milliliters

Other information

- each 5 mL contains: phosphorus 15 mg and sodium18 mg
- safety sealed: do not use if carton is opened or seal under cap opening is broken or missing
- store between 20° to 25°C (68° to 77°F)

Inactive ingredients

art strawberry flavor, dibasic sodium phosphate anhydrous, edetate disodium, ethylparaben, methylparaben, modified food starch (corn), monobasic sodium phosphate, poloxamer 407, propylene glycol, purified water, sucrose, titanium dioxide, triacetin, xanthan gum, xylitol.

Questions or comments?

call 1-855-274-4122 (Monday - Friday 8:30 AM to 5:00 PM EST)

Distributed by:
AUROHEALTH LLC
279 Princeton-Hightstown Road
East Windsor, NJ 08520
Made in India

Code: AP/DRUGS/04/2016

PACKAGE LABEL-PRINCIPAL DISPLAY PANEL - 8 fl. oz.(240 mL Bottle) Container Label

AUROHEALTH

NDC 58602-426-20

Ages 2 Years & Older

NON-DROWSY
Children’s
Fexofenadine Hydrochloride
Oral Suspension
30 mg/5 mL

antihistamine

INDOOR / OUTDOOR ALLERGY RELIEF

Dosing Cup Included
Wash and let air dry
after each use

12 HR
Berry
FLAVOR
Alcohol & Dye FREE
8 fl. oz. (240 mL)

PACKAGE LABEL-PRINCIPAL DISPLAY PANEL - 8 fl. oz. (240 mL Bottle) Carton Container Label

AUROHEALTH

NDC 58602-426-20
#Compare to the active Ingredient
in Children’s Allegra®Allergy

Ages 2 Years & Older

Children’s
Fexofenadine Hydrochloride
Oral Suspension
30 mg/5 mL
antihistamine 12 HR
NON-DROWSY
Liquid

INDOOR / OUTDOOR ALLERGY RELIEF
√ Sneezing
√ Runny Nose
√ Itchy, Watery Eyes
√ Itchy Nose or Throat
Use Only With
Enclosed Dosing Cup
Wash and let air dry after each use

Berry
FLAVOR
Alcohol & Dye FREE

8 fl. oz. (240 mL)